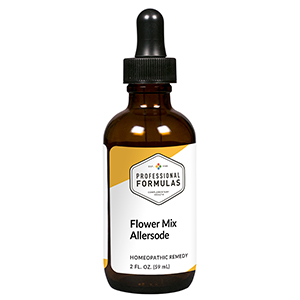 DRUG LABEL: Flowers
NDC: 63083-1008 | Form: LIQUID
Manufacturer: Professional Complementary Health Formulas
Category: homeopathic | Type: HUMAN OTC DRUG LABEL
Date: 20190815

ACTIVE INGREDIENTS: SUS SCROFA ADRENAL GLAND 6 [hp_X]/59 mL; CORTICOTROPIN 6 [hp_X]/59 mL; HISTAMINE DIHYDROCHLORIDE 12 [hp_X]/59 mL; BEEF LIVER 6 [hp_X]/59 mL; SYMPHYOTRICHUM OBLONGIFOLIUM WHOLE 6 [hp_X]/59 mL; CAMELLIA CHEKIANGOLEOSA SEED OIL 6 [hp_X]/59 mL; DIANTHUS CARYOPHYLLUS WHOLE 6 [hp_X]/59 mL; KALIMERIS INDICA WHOLE 6 [hp_X]/59 mL; NARCISSUS POETICUS WHOLE 6 [hp_X]/59 mL; TOWNSENDIA EXSCAPA WHOLE 6 [hp_X]/59 mL; GARDENIA JASMINOIDES FRUIT 6 [hp_X]/59 mL; GENTIANA LUTEA ROOT 6 [hp_X]/59 mL; GLADIOLUS COMMUNIS WHOLE 6 [hp_X]/59 mL; LONICERA CANADENSIS WHOLE 6 [hp_X]/59 mL; C12-17 ALKANE 6 [hp_X]/59 mL; DELPHINIUM AJACIS SEED 6 [hp_X]/59 mL; DIANTHUS SUPERBUS FLOWERING TOP 6 [hp_X]/59 mL; HEDYCHIUM FLAVESCENS WHOLE 6 [hp_X]/59 mL; LUPINUS ELEGANS WHOLE 6 [hp_X]/59 mL; CALENDULA OFFICINALIS FLOWERING TOP 6 [hp_X]/59 mL; NERIUM OLEANDER WHOLE 6 [hp_X]/59 mL; VIOLA TRICOLOR WHOLE 6 [hp_X]/59 mL; PAEONIA X SUFFRUTICOSA SEED 6 [hp_X]/59 mL; RUELLIA SIMPLEX WHOLE 6 [hp_X]/59 mL; ESCHSCHOLZIA CALIFORNICA FLOWERING TOP 6 [hp_X]/59 mL; SEDUM ROSEUM WHOLE 6 [hp_X]/59 mL; ANTIRRHINUM MAJUS LEAF 6 [hp_X]/59 mL; LIRIODENDRON TULIPIFERA WHOLE 6 [hp_X]/59 mL
INACTIVE INGREDIENTS: ALCOHOL; WATER

AROSE

ACTIVE INGREDIENTS

Adrenal 6X
ACTH 6X, 30X
Histaminum hydrochloricum 12X
Liver 6X, 12X
and all the following at 6X, 12X, 60X, 100X:
Aster
Camellia
Carnation
Chrysanthemum
Daffodil
Daisy
Gardenia
Gentian
Gladiola
Honeysuckle
Iris
Larkspur
Lilac
Lily
Lupine
Marigold
Oleander
Pansy
Peony
Petunia
Poppy
Rose
Snapdragon
Tulip

QUESTIONS

Professional Formulas

PO Box 2034 Lake Oswego, OR 97035

INDICATIONS

For the temporary relief of runny nose, sneezing, itching of the nose or throat, and itchy, watery eyes due to sensitivity to flowers.*

PURPOSE

*Claims based on traditional homeopathic practice, not accepted medical evidence. Not FDA evaluated.

WARNINGS

In case of overdose, get medical help or contact a poison control center right away.

Keep out of the reach of children.

PREGNANCY OR BREAST FEEDING

If pregnant or breastfeeding, ask a healthcare professional before use.

DIRECTIONS

Place drops under tongue 30 minutes before/after meals. Adults and children 12 years and over: Take 10 to 15 drops up to 3 times per day. For desensitization, begin with 1 to 5 drops daily, increasing to the standard dose gradually to avoid symptom expression; after 1 to 3 months at the standard dose, decrease gradually to a maintenance dose of 10 to 15 drops weekly. Consult a physician for use in children under 12 years of age.

OTHER INFORMATION

Tamper resistant. If seal is broken, do not use. After opening, close container tightly and store at room temperature away from heat.

INACTIVE INGREDIENTS

20% ethanol, purified water.

LABEL

Est 1985

Professional Formulas

Complementary Health

Flowers

Homeopathic Remedy

2 FL. OZ. (59 mL)